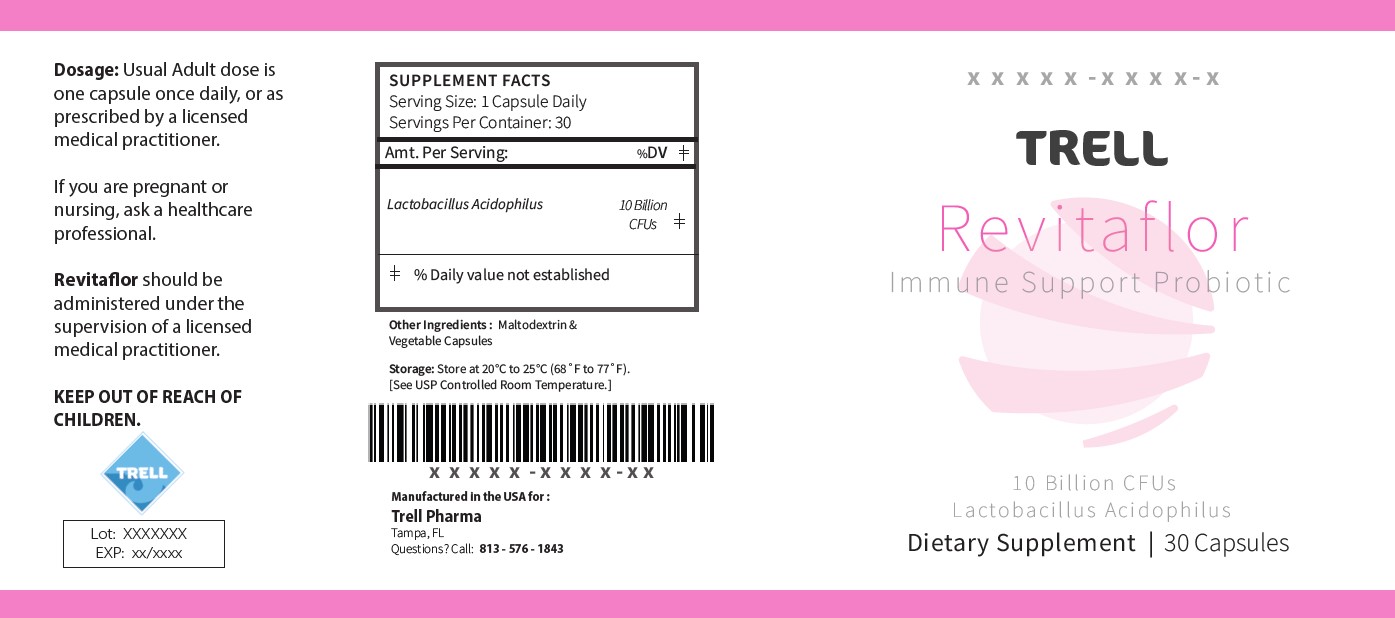 DRUG LABEL: REVITAFLOR
NDC: 82379-8758 | Form: CAPSULE
Manufacturer: Trell Pharma, LLC
Category: other | Type: DIETARY SUPPLEMENT
Date: 20230930

ACTIVE INGREDIENTS: LACTOBACILLUS ACIDOPHILUS 10000000000 [CFU]/1 1
INACTIVE INGREDIENTS: MALTODEXTRIN

REVITAFLOR Capsules
Dietary Supplement

HEALTH CLAIM:

REVITAFLOR Capsules Dietary Supplement
Dispensed by Prescription

Supplement Facts

Serving Size: 1 Capsule Daily

Servings Per Container: 30

Amount Per Serving:

% Daily Value

Probiotic blend

(Lactobacillus acidophilus)

10 billion CFU **

** Daily values not established

Other Ingredients: Maltodextrin, Vegetable Capsules

DESCRIPTION:

REVITAFLOR is an orally administered prescription probiotic formulation for the clinical dietary management of suboptimal nutritional status in patients where advanced supplementation is required and nutritional supplementation in physiologically stressful conditions for maintenance of good health is needed.

REVITAFLOR should be administered under the supervision of a licensed medical practitioner.

WARNINGS AND PRECAUTIONS:

This product is contraindicated in patients with a known hypersensitivity to any of the ingredients.

REVITAFLOR should only be used under the direction and supervision of a licensed medical practitioner. Use with caution in patients that may have a medical condition, are pregnant, lactating, trying to conceive, under the age of 18, or taking medications.

DOSAGE AND ADMINISTRATION:

Usual adult dose is 1 capsule by mouth daily with or without food.

INDICATIONS AND USAGE

REVITAFLOR is an orally administered prescription probiotic formulation for the clinical dietary management of suboptimal nutritional status in patients where advanced supplementation is required and nutritional supplementation in physiologically stressful conditions for maintenance of good health is needed.

HOW SUPPLIED:

REVITAFLOR is supplied as clear capsules dispensed in plastic bottles of 30 ct.

82379-8758-1

Reserved for Professional Recommendation

All prescriptions using this product shall be pursuant to state statutes as applicable. This is not an Orange Book product. This product may be administered only under a physician’s supervision. There are no implied or explicit claims on therapeutic equivalence.

Manufactured for:
Trell Pharma, LLC
Tampa, FL 33626

STORAGE:

Product is sensitive to moisture and heat. Keep bottle tightly closed in a dry, cool place. Store at 20^0C to 25^0C (68^0F to 77^0F).